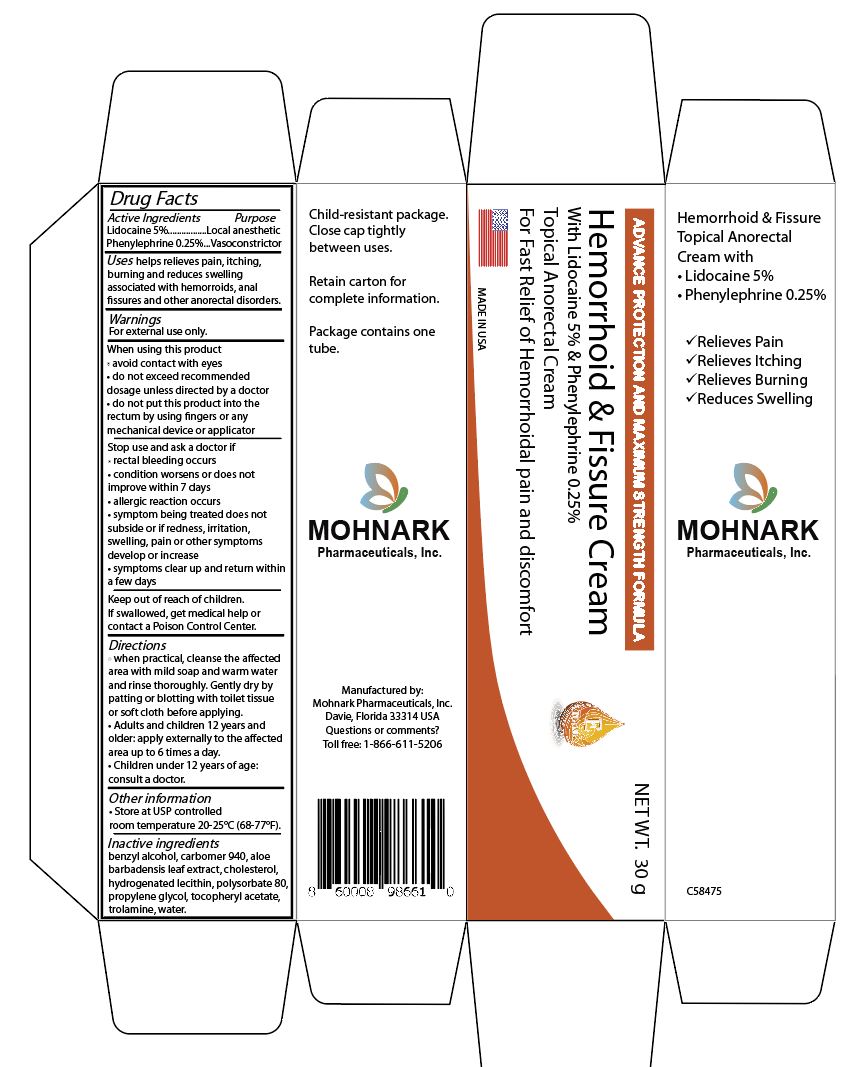 DRUG LABEL: Hemorrhoid and Fissure Cream with Lidocaine 5% plus Phenylephrine HCL 0.25%
NDC: 73715-007 | Form: CREAM
Manufacturer: Mohnark Pharmaceuticals Inc
Category: otc | Type: HUMAN OTC DRUG LABEL
Date: 20250816

ACTIVE INGREDIENTS: PHENYLEPHRINE HYDROCHLORIDE 0.25 g/100 g; LIDOCAINE 5 g/100 g
INACTIVE INGREDIENTS: POLYSORBATE 80 1 g/100 g

Hemorrhoid and Fissure Cream with Lidocaine 5% plus Phenylephrine 0.25%

Active Ingredients

Lidocaine 5%

Phenylephrine HCL 0.25%

Purpose

External Analgesic

Vasoconstrictor

Warnings

For external use only

When using this product

• avoid contact with eyes
• do not exceed recommended
dosage unless directed by a doctor
• do not put this product into the
rectum by using fingers or any
mechanical device or applicato

Stop use and ask a doctor if

• rectal bleeding occurs
• condition worsens or does not
improve within 7 days
• allergic reaction occurs
• symptom being treated does not
subside or if redness, irritation,
swelling, pain or other symptoms
develop or increase
• symptoms clear up and return within
a few days

Keep out of reach of children

If swallowed, get medical help or
contact a Poison Control Center.

Directions

• when practical, cleanse the affected area with mild soap and warm water
and rinse thoroughly. Gently dry by patting or blotting with toilet tissue or soft cloth before applying.
• Adults and children 12 years and older: apply externally to the affected
area up to 6 times a day.
• Children under 12 years of age: consult a doctor.

Other Information

• Store at USP controlled room temperature 20-25°C (68-77°F)

Inactive Ingredients

benzyl alcohol, carbomer 940, aloe
barbadensis leaf extract, cholesterol,
hydrogenated lecithin, polysorbate 80,
propylene glycol, tocopheryl acetate,
trolamine, water.

Uses

- temporary relief of anorectal itching and discomfort associated with hemorrhoids and other anorectal disorders
- for the temporary relief of pain, soreness or burning
- temporarily reduces the swelling associated with hemorrhoids
- temporarily shrinks hemorrhoidal tissue

Dosage and Administration

adults, when practical, cleanse the affected area by pattig or blotting with an appropriate cleansing pad

gently dry by patting or blotting with toie tissue or soft cloth before application of this product

apply externally to the affected area up to 4 times daily

chidren under 12 years of age, consult a doctor

Uses

temporary relief of anorectal itching and discomfort associated with hemorrhoids and other anorectal disorders

for the temporary relief of pain, soreness or burning

temporarily reduces the swelling associated with hemorrhoids

temporarily shrinks hemorrhoidal tissue